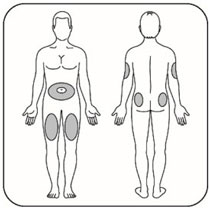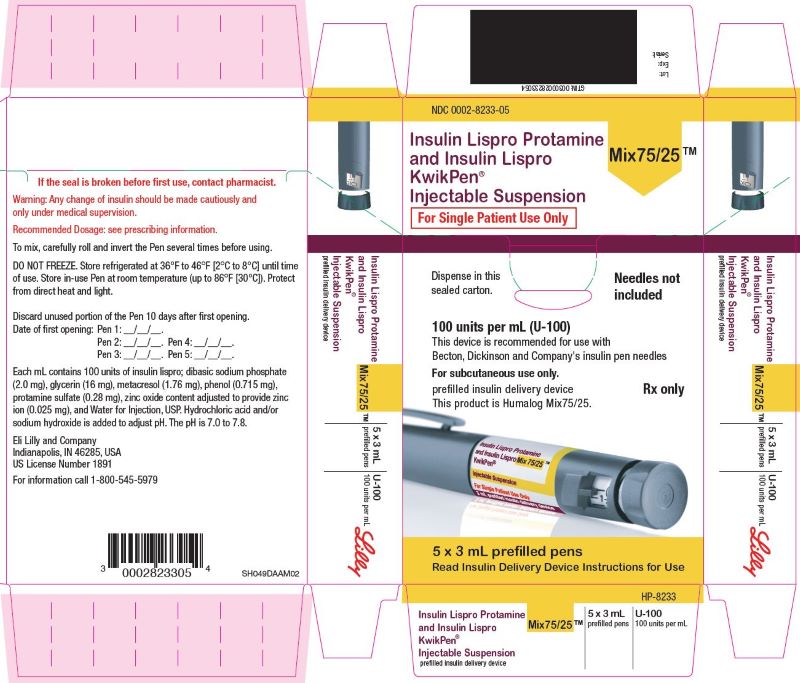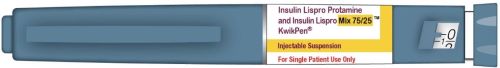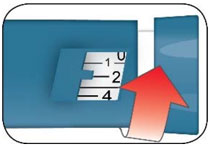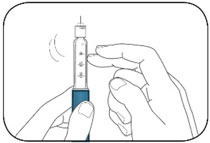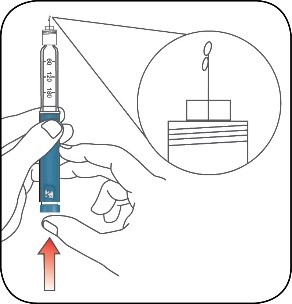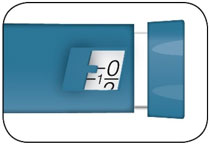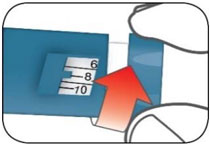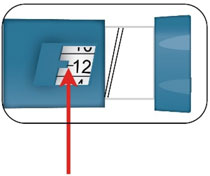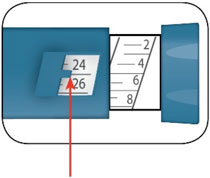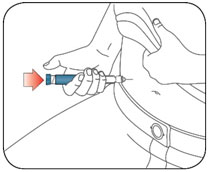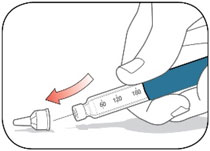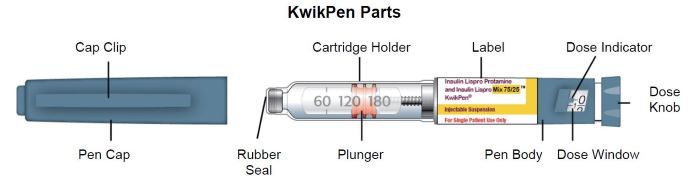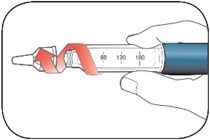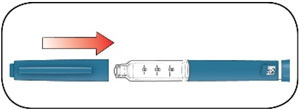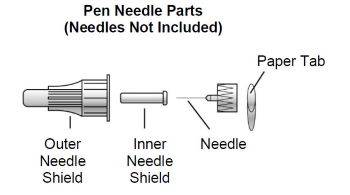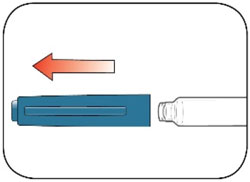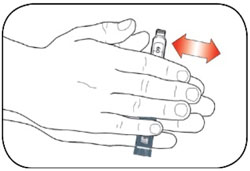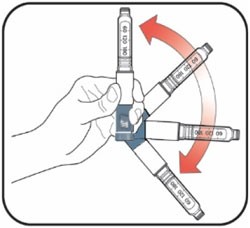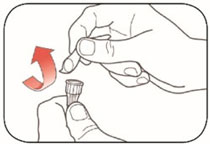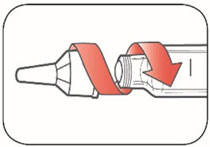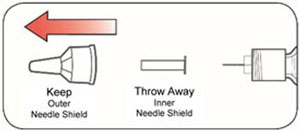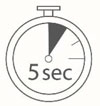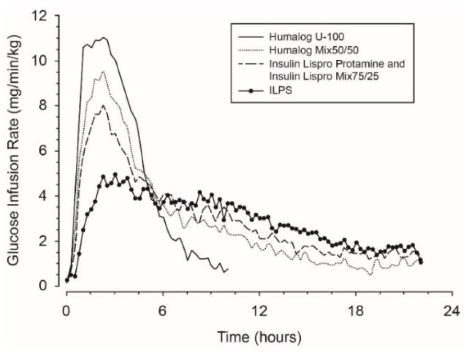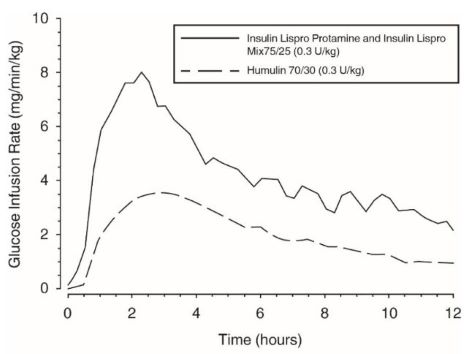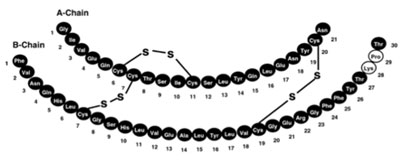 DRUG LABEL: Insulin Lispro Protamine and Insulin Lispro Injectable Suspension
NDC: 0002-8233 | Form: INJECTION, SUSPENSION
Manufacturer: Eli Lilly and Company
Category: prescription | Type: HUMAN PRESCRIPTION DRUG LABEL
Date: 20240806

ACTIVE INGREDIENTS: Insulin lispro 100 [iU]/1 mL
INACTIVE INGREDIENTS: Protamine sulfate 0.28 mg/1 mL; Glycerin 16 mg/1 mL; Sodium Phosphate, Dibasic, Unspecified Form 3.78 mg/1 mL; Metacresol 1.76 mg/1 mL; Zinc oxide .025 mg/1 mL; Phenol .715 mg/1 mL; Water; Hydrochloric acid; Sodium hydroxide

HIGHLIGHTS OF PRESCRIBING INFORMATION

These highlights do not include all the information needed to use INSULIN LISPRO PROTAMINE AND INSULIN LISPRO MIX75/25 safely and effectively. See full prescribing information for INSULIN LISPRO PROTAMINE AND INSULIN LISPRO MIX75/25.
INSULIN LISPRO PROTAMINE AND INSULIN LISPRO injectable suspension Mix75/25, for subcutaneous use
Initial U.S. Approval: 1999
This product is HUMALOG® Mix75/25™ (insulin lispro protamine and insulin lispro).

1 INDICATIONS AND USAGE

Insulin Lispro Protamine and Insulin Lispro Mix75/25™ is a mixture of insulin lispro protamine, an intermediate-acting human insulin analog, and insulin lispro, a rapid-acting human insulin analog indicated to improve glycemic control in adults with diabetes mellitus. (1)

Limitations of Use:

The proportions of rapid-acting and intermediate-acting insulins are fixed and do not allow for basal versus prandial dose adjustments. (1)

2 DOSAGE AND ADMINISTRATION

- See Full Prescribing Information for important preparation and administration instructions. (2.1)
- Inject Insulin Lispro Protamine and Insulin Lispro Mix75/25 subcutaneously within 15 minutes before a meal in abdominal wall, thigh, upper arm, or buttocks and rotate injection sites to reduce the risk of lipodystrophy and localized cutaneous amyloidosis. (2.1, 2.2)
- Individualize and adjust dosage based on metabolic needs, blood glucose monitoring results and glycemic control goal. (2.2)
- Do not administer Insulin Lispro Protamine and Insulin Lispro Mix75/25 intravenously or by a continuous subcutaneous insulin infusion pump. (2.1)
- Insulin Lispro Protamine and Insulin Lispro Mix75/25 is typically dosed twice daily (with each dose intended to cover 2 meals or a meal and a snack). (2.2)

3 DOSAGE FORMS AND STRENGTHS

Injectable suspension: 100 units/mL (U-100) of Insulin Lispro Protamine and Insulin Lispro Mix75/25, 75% insulin lispro protamine and 25% insulin lispro available as: (3)

- 3 mL single-patient-use KwikPen® prefilled pen

4 CONTRAINDICATIONS

- Do not use during episodes of hypoglycemia. (4)
- Do not use in patients with hypersensitivity to Insulin Lispro Protamine and Insulin Lispro Mix75/25 or any of its excipients. (4)

5 WARNINGS AND PRECAUTIONS

- Never share an Insulin Lispro Protamine and Insulin Lispro Mix75/25 KwikPen between patients, even if the needle is changed. (5.1)
- Hyperglycemia or Hypoglycemia with Changes in Insulin Regimen: Make changes to a patient's insulin regimen (e.g., insulin strength, manufacturer, type, injection site or method of administration) under close medical supervision with increased frequency of blood glucose monitoring. (5.2)
- Hypoglycemia: May be life-threatening. Increase frequency of blood glucose monitoring with changes to insulin dosage, co-administered glucose lowering medications, meal pattern, physical activity; in patients with renal or hepatic impairment; and in patients with hypoglycemia unawareness. (5.3)
- Hypoglycemia Due to Medication Errors: Accidental mix-ups between insulin products can occur. Instruct patients to check insulin labels before injection. (5.4)
- Hypersensitivity Reactions: Severe, life-threatening, generalized allergy, including anaphylaxis, can occur. Discontinue Insulin Lispro Protamine and Insulin Lispro Mix75/25, monitor and treat if indicated. (5.5)
- Hypokalemia: May be life-threatening. Monitor potassium levels in patients at risk of hypokalemia and treat if indicated. (5.6)
- Fluid Retention and Heart Failure with Concomitant Use of Thiazolidinediones (TZDs): Observe for signs and symptoms of heart failure; consider dosage reductions or discontinuation if heart failure occurs. (5.7)

6 ADVERSE REACTIONS

Adverse reactions observed with Insulin Lispro Protamine and Insulin Lispro Mix75/25 include hypoglycemia, allergic reactions, injection site reactions, lipodystrophy, weight gain, edema, pruritus, and rash. (6)

To report SUSPECTED ADVERSE REACTIONS, contact Eli Lilly and Company at 1-800-LillyRx (1-800-545-5979) or FDA at 1-800-FDA-1088 or www.fda.gov/medwatch.

7 DRUG INTERACTIONS

- Drugs that may increase the risk of hypoglycemia: antidiabetic agents, ACE inhibitors, angiotensin II receptor blocking agents, disopyramide, fibrates, fluoxetine, monoamine oxidase inhibitors, pentoxifylline, pramlintide, salicylates, somatostatin analog (e.g., octreotide), and sulfonamide antibiotics. (7)
- Drugs that may decrease the blood glucose lowering effect: atypical antipsychotics, corticosteroids, danazol, diuretics, estrogens, glucagon, isoniazid, niacin, oral contraceptives, phenothiazines, progestogens (e.g., in oral contraceptives), protease inhibitors, somatropin, sympathomimetic agents (e.g., albuterol, epinephrine, terbutaline), and thyroid hormones. (7)
- Drugs that may increase or decrease the blood glucose lowering effect: alcohol, beta-blockers, clonidine, lithium salts, and pentamidine. (7)
- Drugs that may blunt the signs and symptoms of hypoglycemia: beta-blockers, clonidine, guanethidine, and reserpine. (7)

FULL PRESCRIBING INFORMATION

1 INDICATIONS AND USAGE

Insulin Lispro Protamine and Insulin Lispro Mix75/25 is indicated to improve glycemic control in adults with diabetes mellitus.

Limitations of Use:

The proportions of rapid-acting and intermediate-acting insulins in Insulin Lispro Protamine and Insulin Lispro Mix75/25 are fixed and do not allow for basal versus prandial dose adjustments.

2 DOSAGE AND ADMINISTRATION

2.1 Important Preparation and Administration Instructions

Preparation Instructions

- Always check insulin labels before administration. This product is HUMALOG Mix75/25 [see Warnings and Precautions (5.4)].
- Insulin Lispro Protamine and Insulin Lispro Mix75/25 is a suspension that must be resuspended immediately before use. Resuspension is easier when the insulin has reached room temperature.
- To resuspend KwikPen, gently roll the KwikPen at least 10 times and then carefully invert the KwikPen at least 10 times until the suspension appears uniformly white and cloudy.
- Inspect Insulin Lispro Protamine and Insulin Lispro Mix75/25 visually before use. Do not use if discoloration or particulate matter is seen.

Administration Instructions

- After resuspension, immediately administer Insulin Lispro Protamine and Insulin Lispro Mix75/25 by subcutaneous injection into the abdominal wall, thigh, upper arm, or buttocks.
- Rotate the injection site within the same region from one injection to the next to reduce the risk of lipodystrophy and localized cutaneous amyloidosis. Do not inject into areas of lipodystrophy or localized cutaneous amyloidosis [see Warnings and Precautions (5.2) and Adverse Reactions (6)].
- The Insulin Lispro Protamine and Insulin Lispro Mix75/25 KwikPen dials in 1 unit increments. Use Insulin Lispro Protamine and Insulin Lispro Mix75/25 KwikPen with caution in patients with visual impairment that may rely on audible clicks to dial their dose.
- Do not administer Insulin Lispro Protamine and Insulin Lispro Mix75/25 intravenously or by a continuous subcutaneous insulin infusion pump.
- Do not mix Insulin Lispro Protamine and Insulin Lispro Mix75/25 with any other insulins or diluents.

2.2 Dosage Recommendations

- Individualize and adjust the dosage of Insulin Lispro Protamine and Insulin Lispro Mix75/25 based on the individual's metabolic needs, blood glucose monitoring results and glycemic control goal.
- Inject Insulin Lispro Protamine and Insulin Lispro Mix75/25 subcutaneously within 15 minutes before a meal.
- Insulin Lispro Protamine and Insulin Lispro Mix75/25 is typically dosed twice-daily (with each dose intended to cover 2 meals or a meal and a snack).
- Dosage adjustments may be needed with changes in physical activity, changes in meal patterns (i.e., macronutrient content or timing of food intake), changes in renal or hepatic function or during acute illness [see Warnings and Precautions (5.2, 5.3) and Use in Specific Populations (8.6, 8.7)].
- When switching from another insulin to Insulin Lispro Protamine and Insulin Lispro Mix75/25, a different dosage of Insulin Lispro Protamine and Insulin Lispro Mix75/25 may be needed.
- During changes to a patient's insulin regimen, increase the frequency of blood glucose monitoring [see Warnings and Precautions (5.2)].

2.3 Dosage Modifications for Drug Interactions

Dosage modification may be needed when Insulin Lispro Protamine and Insulin Lispro Mix75/25 is used concomitantly with certain drugs [see Drug Interactions (7)].

3 DOSAGE FORMS AND STRENGTHS

Injectable Suspension: 100 units/mL (U-100) of Insulin Lispro Protamine and Insulin Lispro, 75% insulin lispro protamine and 25% insulin lispro is a white and cloudy suspension available as:

- 3 mL single-patient-use KwikPen prefilled pen

4 CONTRAINDICATIONS

Insulin Lispro Protamine and Insulin Lispro Mix75/25 is contraindicated:

- during episodes of hypoglycemia [see Warnings and Precautions (5.3)]
- in patients who have had hypersensitivity reactions to Insulin Lispro Protamine and Insulin Lispro Mix75/25 or to any of its excipients. [see Warnings and Precautions (5.5)]

5 WARNINGS AND PRECAUTIONS

5.1 Never Share an Insulin Lispro Protamine and Insulin Lispro Mix75/25 KwikPen Between Patients

Insulin Lispro Protamine and Insulin Lispro Mix75/25 KwikPens must never be shared between patients, even if the needle is changed. Sharing poses a risk for transmission of blood-borne pathogens.

5.2 Hyperglycemia or Hypoglycemia with Changes in Insulin Regimen

Changes in an insulin regimen (e.g., insulin strength, manufacturer, type, injection site or method of administration) may affect glycemic control and predispose to hypoglycemia [see Warnings and Precautions (5.3)] or hyperglycemia. Repeated insulin injections into areas of lipodystrophy or localized cutaneous amyloidosis have been reported to result in hyperglycemia; and a sudden change in the injection site (to an unaffected area) has been reported to result in hypoglycemia [see Adverse Reactions (6)].

Make any changes to a patient's insulin regimen under close medical supervision with increased frequency of blood glucose monitoring. Advise patients who have repeatedly injected into areas of lipodystrophy or localized cutaneous amyloidosis to change the injection site to unaffected areas and closely monitor for hypoglycemia. For patients with type 2 diabetes, dosage adjustments of concomitant anti-diabetic products may be needed.

5.3 Hypoglycemia

Hypoglycemia is the most common adverse reaction associated with all insulins, including Insulin Lispro Protamine and Insulin Lispro Mix75/25. Severe hypoglycemia can cause seizures, may lead to unconsciousness, may be life-threatening, or cause death. Hypoglycemia can impair concentration ability and reaction time; this may place an individual and others at risk in situations where these abilities are important (e.g., driving or operating other machinery).

Hypoglycemia can happen suddenly, and symptoms may differ in each individual and change over time in the same individual. Symptomatic awareness of hypoglycemia may be less pronounced in patients with longstanding diabetes, in patients with diabetic nerve disease, in patients using medications that block the sympathetic nervous system (e.g., beta-blockers) [see Drug Interactions (7)], or in patients who experience recurrent hypoglycemia.

Risk Factors for Hypoglycemia

The risk of hypoglycemia after an injection is related to the duration of action of the insulin and in general, is highest when the glucose lowering effect of the insulin is maximal. As with all insulins, the glucose lowering effect time course of Insulin Lispro Protamine and Insulin Lispro Mix75/25 may vary in different individuals or at different times in the same individual and depends on many conditions, including the area of injection as well as the injection site blood supply and temperature [see Clinical Pharmacology (12.2)]. Other factors which may increase the risk of hypoglycemia include changes in meal pattern (e.g., macronutrient content or timing of meals), changes in level of physical activity, or changes to co-administered medication [see Drug Interactions (7)]. Patients with renal or hepatic impairment may be at higher risk of hypoglycemia [see Use in Specific Populations (8.6, 8.7)].

Risk Mitigation Strategies for Hypoglycemia

Patients and caregivers must be educated to recognize and manage hypoglycemia. Self-monitoring of blood glucose plays an essential role in the prevention and management of hypoglycemia. In patients at higher risk for hypoglycemia and patients who have reduced symptomatic awareness of hypoglycemia, increased frequency of blood glucose monitoring is recommended.

5.4 Hypoglycemia Due to Medication Errors

Accidental mix-ups between insulin products have been reported. To avoid medication errors between Insulin Lispro Protamine and Insulin Lispro Mix75/25 and other insulins, instruct patients to always check the insulin label before each injection.

5.5 Hypersensitivity Reactions

Severe, life-threatening, generalized allergy, including anaphylaxis, can occur with insulins, including Insulin Lispro Protamine and Insulin Lispro Mix75/25. If hypersensitivity reactions occur, discontinue Insulin Lispro Protamine and Insulin Lispro Mix75/25; treat per standard of care and monitor until symptoms and signs resolve. Insulin Lispro Protamine and Insulin Lispro Mix75/25 is contraindicated in patients who have had hypersensitivity reactions to Insulin Lispro Protamine and Insulin Lispro Mix75/25 or any of its excipients [see Contraindications (4)].

5.6 Hypokalemia

All insulins, including Insulin Lispro Protamine and Insulin Lispro Mix75/25, cause a shift in potassium from the extracellular to intracellular space, possibly leading to hypokalemia. Untreated hypokalemia may cause respiratory paralysis, ventricular arrhythmia, and death. Monitor potassium levels in patients at risk for hypokalemia if indicated (e.g., patients using potassium-lowering medications, patients taking medications sensitive to serum potassium concentrations).

5.7 Fluid Retention and Heart Failure with Concomitant Use of PPAR-gamma Agonists

Thiazolidinediones (TZDs), which are peroxisome proliferator-activated receptor (PPAR)-gamma agonists, can cause dose-related fluid retention, particularly when used in combination with insulin. Fluid retention may lead to or exacerbate heart failure. Patients treated with insulin, including Insulin Lispro Protamine and Insulin Lispro Mix75/25, and a PPAR-gamma agonist should be observed for signs and symptoms of heart failure. If heart failure develops, it should be managed according to current standards of care, and discontinuation or dose reduction of the PPAR-gamma agonist must be considered.

6 ADVERSE REACTIONS

The following adverse reactions are discussed elsewhere in the labeling:

- Hypoglycemia [see Warnings and Precautions (5.3)]
- Hypoglycemia Due to Medication Errors [see Warnings and Precautions (5.4)]
- Hypersensitivity Reactions [see Warnings and Precautions (5.5)]
- Hypokalemia [see Warnings and Precautions (5.6)]

Adverse Reactions from Clinical Studies or Postmarketing Reports

The following adverse reactions have been identified during post-marketing use of Insulin Lispro Protamine and Insulin Lispro Mix75/25. Because some of these reactions are reported voluntarily from a population of uncertain size, it is not always possible to reliably estimate their frequency or establish a causal relationship to drug exposure.

Adverse reactions associated with insulin initiation and glucose control intensification

Intensification or rapid improvement in glucose control has been associated with a transitory, reversible ophthalmologic refraction disorder, worsening of diabetic retinopathy, and acute painful peripheral neuropathy. Over the long-term, improved glycemic control decreases the risk of diabetic retinopathy and neuropathy.

Hypersensitivity reactions

Severe, life-threatening, generalized allergy, including anaphylaxis.

Hypoglycemia

Hypoglycemia is the most commonly observed adverse reaction in Insulin Lispro Protamine and Insulin Lispro Mix75/25.

Hypokalemia

Insulin Lispro Protamine and Insulin Lispro Mix75/25 can cause a shift in potassium from the extracellular to intracellular space, possibly leading to hypokalemia.

Injection site reactions

Insulin Lispro Protamine and Insulin Lispro Mix75/25 can cause local injection site reactions including redness, swelling, or itching at the site of injection. These reactions usually resolve in a few days to a few weeks, but in some occasions, may require discontinuation. Localized reactions and generalized myalgias have been reported with the use of meta-cresol, which is an excipient in Insulin Lispro Protamine and Insulin Lispro Mix75/25.

Lipodystrophy

Administration of insulin subcutaneously, including Insulin Lispro Protamine and Insulin Lispro Mix75/25, has resulted in lipoatrophy (depression in the skin) or lipohypertrophy (enlargement or thickening of tissue) [see Dosage and Administration (2.1)] in some patients.

Localized cutaneous amyloidosis

Localized cutaneous amyloidosis at the injection site has occurred. Hyperglycemia has been reported with repeated insulin injections into areas of localized cutaneous amyloidosis; hypoglycemia has been reported with a sudden change to an unaffected injection site.

Medication Errors

Medication errors in which other insulins have been accidentally substituted for Insulin Lispro Protamine and Insulin Lispro Mix75/25 have been identified during postapproval use.

Peripheral Edema

Insulins, including Insulin Lispro Protamine and Insulin Lispro Mix75/25, may cause sodium retention and edema, particularly if previously poor metabolic control is improved by intensified insulin therapy.

Weight gain

Weight gain can occur with insulins, including Insulin Lispro Protamine and Insulin Lispro Mix75/25, and has been attributed to the anabolic effects of insulin and the decrease in glycosuria.

Immunogenicity

As with all therapeutic proteins, insulin administration may cause anti-insulin antibodies to form. The incidence of antibody formation with Insulin Lispro Protamine and Insulin Lispro Mix75/25 is unknown.

7 DRUG INTERACTIONS

Table 1 below presents clinically significant drug interactions with Insulin Lispro Protamine and Insulin Lispro Mix75/25.

Table 1: Clinically Significant Drug Interactions with Insulin Lispro Protamine and Insulin Lispro Mix75/25
Drugs that May Increase the Risk of Hypoglycemia
Drugs: | Antidiabetic agents, ACE inhibitors, angiotensin II receptor blocking agents, disopyramide, fibrates, fluoxetine, monoamine oxidase inhibitors, pentoxifylline, pramlintide, salicylates, somatostatin analog (e.g., octreotide), and sulfonamide antibiotics.
Intervention: | Dose adjustment and increased frequency of glucose monitoring may be required when Insulin Lispro Protamine and Insulin Lispro Mix75/25 is co-administered with these drugs.
Drugs that May Decrease the Blood Glucose Lowering Effect of Insulin Lispro Protamine and Insulin Lispro Mix75/25
Drugs: | Atypical antipsychotics (e.g., olanzapine and clozapine), corticosteroids, danazol, diuretics, estrogens, glucagon, isoniazid, niacin, oral contraceptives, phenothiazines, progestogens (e.g., in oral contraceptives), protease inhibitors, somatropin, sympathomimetic agents (e.g., albuterol, epinephrine, terbutaline), and thyroid hormones.
Intervention: | Dose adjustment and increased frequency of glucose monitoring may be required when Insulin Lispro Protamine and Insulin Lispro Mix75/25 is co-administered with these drugs.
Drugs that May Increase or Decrease the Blood Glucose Lowering Effect of Insulin Lispro Protamine and Insulin Lispro Mix75/25
Drugs: | Alcohol, beta-blockers, clonidine, and lithium salts. Pentamidine may cause hypoglycemia, which may sometimes be followed by hyperglycemia.
Intervention: | Dose adjustment and increased frequency of glucose monitoring may be required when Insulin Lispro Protamine and Insulin Lispro Mix75/25 is co-administered with these drugs.
Drugs that May Blunt Signs and Symptoms of Hypoglycemia
Drugs: | Beta-blockers, clonidine, guanethidine, and reserpine.
Intervention: | Increased frequency of glucose monitoring may be required when Insulin Lispro Protamine and Insulin Lispro Mix75/25 is co-administered with these drugs.

8 USE IN SPECIFIC POPULATIONS

8.1 Pregnancy

Risk Summary

Published studies with insulin lispro used during pregnancy have not reported an association between insulin lispro and the induction of major birth defects, miscarriage, or adverse maternal or fetal outcomes (see Data). There are risks to the mother and fetus associated with poorly controlled diabetes in pregnancy (see Clinical Considerations).

Pregnant rats and rabbits were exposed to insulin lispro in animal reproduction studies during organogenesis. No adverse effects on embryo/fetal viability or morphology were observed in offspring of rats exposed to insulin lispro at a dose approximately 3 times the human subcutaneous dose of 1 unit insulin lispro/kg/day. No adverse effects on embryo/fetal development were observed in offspring of rabbits exposed to insulin lispro at doses up to approximately 0.2 times the human subcutaneous dose of 1 unit/kg/day (see Data).

The estimated background risk of major birth defects is 6-10% in women with pre-gestational diabetes with a HbA1c >7 and has been reported to be as high as 20-25% in women with a HbA1c >10. The estimated background risk of miscarriage for the indicated population is unknown. In the U.S. general population, the estimated background risk of major birth defects and miscarriage in clinically recognized pregnancies is 2-4% and 15-20%, respectively.

Clinical Considerations

Disease-associated maternal and/or embryo/fetal risk

Poorly controlled diabetes in pregnancy increases the maternal risk for diabetic ketoacidosis, pre-eclampsia, spontaneous abortions, preterm delivery, and delivery complications. Poorly controlled diabetes increases the fetal risk for major birth defects, still birth, and macrosomia related morbidity.

Data

Human Data

Published data from retrospective studies and meta-analyses do not report an association with insulin lispro and major birth defects, miscarriage, or adverse maternal or fetal outcomes when insulin lispro is used during pregnancy. However, these studies cannot definitely establish or exclude the absence of any risk because of methodological limitations including small sample size, selection bias, confounding by unmeasured factors, and some lacking comparator groups.

Animal Data

Animal reproduction studies have not been performed with Insulin Lispro Protamine and Insulin Lispro Mix75/25. However, subcutaneous reproduction and teratology studies have been conducted with insulin lispro (a component of Insulin Lispro Protamine and Insulin Lispro Mix75/25). In a combined fertility and embryo-fetal development study, female rats were given subcutaneous insulin lispro injections of 1, 5, and 20 units/kg/day (0.2, 0.8, and 3 times the human subcutaneous dose of 1 unit insulin lispro/kg/day, based on units/body surface area, respectively) from 2 weeks prior to cohabitation through Gestation Day 19. There were no adverse effects on female fertility, implantation, or fetal viability and morphology. However, fetal growth retardation was produced at the 20 units/kg/day-dose as indicated by decreased fetal weight and an increased incidence of fetal runts/litter.

In an embryo-fetal development study in pregnant rabbits, insulin lispro doses of 0.1, 0.25, and 0.75 unit/kg/day (0.03, 0.08, and 0.2 times the human subcutaneous dose of 1 unit insulin lispro/kg/day, based on units/body surface area, respectively) were injected subcutaneously on Gestation days 7 through 19. There were no adverse effects on fetal viability, weight, and morphology at any dose.

8.2 Lactation

Risk Summary

Available data from published literature suggests that exogenous human insulin products, including Insulin Lispro Protamine and Insulin Lispro Mix75/25, are transferred into human milk. There are no adverse reactions reported in breastfed infants in the literature. There are no data on the effects of exogenous human insulin products, including Insulin Lispro Protamine and Insulin Lispro Mix75/25, on milk production. The developmental and health benefits of breastfeeding should be considered along with the mother's clinical need for insulin, any potential adverse effects on the breastfed child from Insulin Lispro Protamine and Insulin Lispro Mix75/25 or from the underlying maternal condition.

8.4 Pediatric Use

Safety and effectiveness of Insulin Lispro Protamine and Insulin Lispro Mix75/25 in pediatric patients have not been established.

8.5 Geriatric Use

Clinical studies of Insulin Lispro Protamine and Insulin Lispro Mix75/25 did not include sufficient numbers of patients aged 65 and over to determine whether they respond differently than younger patients. In patients aged 65 and over with diabetes, the initial dosing, dose increments, and maintenance dosage should be conservative to reduce the risk of hypoglycemia [see Warnings and Precautions (5.3)].

8.6 Renal Impairment

The effect of renal impairment on the pharmacokinetics of Insulin Lispro Protamine and Insulin Lispro Mix75/25 has not been studied. Patients with renal impairment may be at increased risk of hypoglycemia and may require more frequent Insulin Lispro Protamine and Insulin Lispro Mix75/25 dose adjustment and more frequent glucose monitoring [see Warnings and Precautions (5.3)].

8.7 Hepatic Impairment

The effect of hepatic impairment on the pharmacokinetics of Insulin Lispro Protamine and Insulin Lispro Mix75/25 has not been studied. Patients with hepatic impairment may be at increased risk of hypoglycemia and may require more frequent Insulin Lispro Protamine and Insulin Lispro Mix75/25 dose adjustment and more frequent glucose monitoring [see Warnings and Precautions (5.3)].

10 OVERDOSAGE

Excess insulin administration may cause hypoglycemia and hypokalemia. Mild episodes of hypoglycemia usually can be treated with oral glucose. Adjustments in drug dosage, meal patterns, or exercise may be needed. More severe episodes with coma, seizure, or neurologic impairment may be treated with a glucagon product for emergency use or concentrated intravenous glucose. Sustained carbohydrate intake and observation may be necessary because hypoglycemia may recur after apparent clinical recovery. Hypokalemia must be corrected appropriately [see Warnings and Precautions (5.3, 5.6)].

11 DESCRIPTION

Insulin lispro is a rapid-acting insulin analog produced by recombinant DNA technology utilizing a non-pathogenic laboratory strain of Escherichia coli. Insulin lispro differs from human insulin in that the amino acid proline at position B28 is replaced by lysine and the lysine in position B29 is replaced by proline. Chemically, it is Lys(B28), Pro(B29) human insulin analog and has the empirical formula C257H383N65O77S6 and a molecular weight of 5.808 kDa, both identical to that of human insulin.

Insulin Lispro Protamine and Insulin Lispro Mix75/25 is a mixture of 75% insulin lispro protamine, an intermediate-acting human insulin analog, and 25% insulin lispro, a rapid-acting human insulin analog. Insulin lispro protamine suspension is a suspension of crystals produced from combining insulin lispro and protamine sulfate under appropriate conditions for crystal formation.

Insulin lispro has the following primary structure:

Insulin Lispro Protamine and Insulin Lispro Mix75/25 injectable suspension is a white and cloudy, sterile suspension for subcutaneous use.

Each mL of Insulin Lispro Protamine and Insulin Lispro Mix75/25 contains 100 units of insulin lispro; dibasic sodium phosphate (2.0 mg), glycerin (16 mg), metacresol (1.76 mg), phenol (0.715 mg), protamine sulfate (0.28 mg), zinc oxide content adjusted to provide zinc ion (0.025 mg), and Water for Injection, USP. The pH is 7.0 to 7.8. Sodium hydroxide and/or hydrochloric acid is added during manufacture to adjust the pH.

12 CLINICAL PHARMACOLOGY

12.1 Mechanism of Action

The primary activity of insulin, including Insulin Lispro Protamine and Insulin Lispro Mix75/25, is the regulation of glucose metabolism. Insulins lower blood glucose by stimulating peripheral glucose uptake by skeletal muscle and fat, and by inhibiting hepatic glucose production. Insulins inhibit lipolysis and proteolysis, and enhance protein synthesis.

12.2 Pharmacodynamics

In a glucose clamp study performed in 30 healthy subjects, the onset of action and glucose-lowering activity of HUMALOG, HUMALOG® Mix50/50™, Insulin Lispro Protamine and Insulin Lispro Mix75/25, and insulin lispro protamine suspension (ILPS) were compared (see Figure 1). Graphs of mean glucose infusion rate versus time showed a distinct insulin activity profile for each formulation. The rapid onset of glucose-lowering activity characteristic of HUMALOG was maintained in Insulin Lispro Protamine and Insulin Lispro Mix75/25. The median maximum pharmacologic effect of Insulin Lispro Protamine and Insulin Lispro Mix75/25 after administration of a 0.3 unit/kg dose to healthy subjects occurred at approximately 2 hours (range: 1-6 hours); glucose lowering activity was detectable for a median of 22 hours (range: 13 to 22 hours), which was the end of the clamp.

In separate glucose clamp studies performed in healthy subjects, pharmacodynamics of Insulin Lispro Protamine and Insulin Lispro Mix75/25 and HUMULIN® 70/30 were assessed and are presented in Figure 2. Insulin Lispro Protamine and Insulin Lispro Mix75/25 has a duration of activity similar to that of HUMULIN 70/30.

Figures 1 and 2 should be considered only as representative examples since the time course of action of insulin and insulin analogs, may vary in different individuals or within the same individual.

Figure 1: Mean Insulin Activity Versus Time Profiles After Injection of 0.3 units/kg of HUMALOG, HUMALOG Mix50/50, Insulin Lispro Protamine and Insulin Lispro Mix75/25, or Insulin Lispro Protamine Suspension (ILPS) in 30 Healthy Subjects.

Figure 2: Mean Insulin Activity Versus Time Profiles After Injection of 0.3 units/kg of Insulin Lispro Protamine and Insulin Lispro Mix75/25 or HUMULIN 70/30 in Healthy Subjects.

12.3 Pharmacokinetics

Absorption — Insulin Lispro Protamine and Insulin Lispro Mix75/25 has two phases of absorption. The early phase represents insulin lispro and its distinct characteristics of rapid onset. The late phase represents the prolonged absorption of insulin lispro protamine suspension.

In 31 healthy subjects given subcutaneous doses (0.3 unit/kg) of Insulin Lispro Protamine and Insulin Lispro Mix75/25, the median peak serum concentration was 60 minutes (range: 30 minutes to 4 hours) after dosing. Identical results were found in patients with type 1 diabetes. The rapid absorption characteristics of HUMALOG are maintained with Insulin Lispro Protamine and Insulin Lispro Mix75/25. Insulin Lispro Protamine and Insulin Lispro Mix75/25 has a more rapid absorption than HUMULIN 70/30, which has been confirmed in patients with type 1 diabetes.

Metabolism — Human metabolism studies of Insulin Lispro Protamine and Insulin Lispro Mix75/25 have not been conducted. However, studies in animals indicate that the metabolism of HUMALOG, the rapid-acting component of Insulin Lispro Protamine and Insulin Lispro Mix75/25, is identical to that of regular human insulin.

Elimination — Because of the absorption-rate limited kinetics of insulin mixtures, a true half-life cannot be accurately estimated from the terminal slope of the concentration versus time curve.

Specific Populations

The effects of age, race, obesity, pregnancy, smoking, or renal or hepatic impairment on the pharmacokinetics of Insulin Lispro Protamine and Insulin Lispro Mix75/25 have not been studied.

Gender — Pharmacokinetic and pharmacodynamic comparisons between men and women administered Insulin Lispro Protamine and Insulin Lispro Mix75/25 showed no gender differences.

13 NONCLINICAL TOXICOLOGY

13.1 Carcinogenesis, Mutagenesis, Impairment of Fertility

Standard 2-year carcinogenicity studies in animals have not been performed with Insulin Lispro Protamine and Insulin Lispro Mix75/25. In Fischer 344 rats, a 12-month repeat-dose toxicity study was conducted with insulin lispro (a component of Insulin Lispro Protamine and Insulin Lispro Mix75/25) at subcutaneous doses of 20 and 200 units/kg/day (approximately 3 and 32 times the human subcutaneous dose of 1 unit insulin lispro/kg/day, based on units/body surface area). Insulin lispro did not produce important target organ toxicity including mammary tumors at any dose.

Insulin lispro was not mutagenic in the following genetic toxicity assays: bacterial mutation, unscheduled DNA synthesis, mouse lymphoma, chromosomal aberration and micronucleus assays.

Male fertility was not compromised when male rats given subcutaneous insulin lispro injections of 5 and 20 units/kg/day (0.8 and 3 times the human subcutaneous dose of 1 unit insulin lispro/kg/day, based on units/body surface area) for 6 months were mated with untreated female rats. In a combined fertility, perinatal, and postnatal study in male and female rats given 1, 5, and 20 units/kg/day subcutaneously (0.2, 0.8, and 3 times the human subcutaneous dose of 1 unit insulin lispro/kg/day, based on units/body surface area), mating and fertility were not adversely affected in either gender at any dose.

16 HOW SUPPLIED/STORAGE AND HANDLING

16.1 How Supplied

Insulin Lispro Protamine and Insulin Lispro, injectable suspension, is a white and cloudy suspension of 100 units/mL (U-100) of 75% insulin lispro protamine and 25% insulin lispro available as:

3 mL single-patient-use KwikPen prefilled pen | NDC 0002-8233-05

Insulin Lispro Protamine and Insulin Lispro Mix75/25 KwikPens must never be shared between patients, even if the needle is changed. Always use a new needle for each injection to prevent contamination.

The Insulin Lispro Protamine and Insulin Lispro Mix75/25 KwikPen dials in 1 unit increments.

16.2 Storage and Handling

Dispense in the original sealed carton with the enclosed Instructions for Use.

Protect from direct heat and light. Do not freeze and do not use if it has been frozen. See storage table below:

 | Not In-Use (Unopened) Refrigerated (36° to 46°F [2° to 8°C]) | Not In Use (Unopened) Room Temperature (up to 86°F [30°C]) | In-Use (Opened) (see temperature below)
3 mL single-patient-use KwikPen | Until expiration date | 10 days | 10 days Room temperature only (Do not refrigerate)

17 PATIENT COUNSELING INFORMATION

Advise the patient to read the FDA-approved patient labeling (Patient Information and Instructions for Use).

Never Share an Insulin Lispro Protamine and Insulin Lispro Mix75/25 KwikPen Between Patients

Advise patients using Insulin Lispro Protamine and Insulin Lispro Mix75/25 KwikPens not to share needles or KwikPens with another person. Sharing poses a risk for transmission of blood-borne pathogens [see Warnings and Precautions (5.1)].

Hyperglycemia or Hypoglycemia

Inform patients that hypoglycemia is the most common adverse reaction with insulin. Instruct patients on self-management procedures including glucose monitoring, proper injection technique, and management of hypoglycemia and hyperglycemia, especially at initiation of Insulin Lispro Protamine and Insulin Lispro Mix75/25 therapy. Instruct patients on handling of special situations such as intercurrent conditions (illness, stress, or emotional disturbances), an inadequate or skipped insulin dose, inadvertent administration of an increased insulin dose, inadequate food intake, and skipped meals. Instruct patients on the management of hypoglycemia [see Warnings and Precautions (5.3)].

Inform patients that their ability to concentrate and react may be impaired as a result of hypoglycemia. Advise patients who have frequent hypoglycemia or reduced or absent warning signs of hypoglycemia to use caution when driving or operating machinery.

Advise patients that changes in insulin regimen can predispose to hyperglycemia or hypoglycemia and that changes in insulin regimen should be made under close medical supervision [see Warnings and Precautions (5.2)].

Hypoglycemia due to Medication Errors

Instruct patients to always check the insulin label before each injection to avoid mix-ups between insulin products [see Warnings and Precautions (5.4)].

Hypersensitivity Reactions

Advise patients that hypersensitivity reactions have occurred with Insulin Lispro Protamine and Insulin Lispro Mix75/25. Inform patients on the symptoms of hypersensitivity reactions and to seek medical attention if they occur [see Warnings and Precautions (5.5)].

Manufactured by:

Eli Lilly and Company

Indianapolis, IN 46285, USA

US License Number 1891

Humalog® Mix75/25™ and KwikPen® are trademarks of Eli Lilly and Company.

Copyright © 1999, 2023, Eli Lilly and Company. All rights reserved.

ILPILIS7525-0002-USPI-20230721

PATIENT PACKAGE INSERT

PATIENT INFORMATION
Insulin Lispro Protamine and Insulin Lispro [IHN-soo-lihn LIYS-proh]
injectable suspension, for subcutaneous use
This product is HUMALOG® Mix75/25™ (insulin lispro protamine and insulin lispro).

Do not share your Insulin Lispro Protamine and Insulin Lispro Mix75/25 KwikPen with other people, even if the needle has been changed. You may give other people a serious infection or get a serious infection from them.

What is Insulin Lispro Protamine and Insulin Lispro Mix75/25?

- Insulin Lispro Protamine and Insulin Lispro Mix75/25 is a man-made insulin that is used to control high blood sugar in adults with diabetes mellitus.
- It is not known if Insulin Lispro Protamine and Insulin Lispro Mix75/25 is safe and effective in children under 18 years of age.

Who should not take Insulin Lispro Protamine and Insulin Lispro Mix75/25?
Do not take Insulin Lispro Protamine and Insulin Lispro Mix75/25 if you:

- are having an episode of low blood sugar (hypoglycemia).
- have an allergy to Insulin Lispro Protamine and Insulin Lispro Mix75/25 or any of the ingredients in Insulin Lispro Protamine and Insulin Lispro Mix75/25. See the end of this Patient Information leaflet for a complete list of ingredients in Insulin Lispro Protamine and Insulin Lispro Mix75/25.

What should I tell my healthcare provider before taking Insulin Lispro Protamine and Insulin Lispro Mix75/25?
Before taking Insulin Lispro Protamine and Insulin Lispro Mix75/25, tell your healthcare provider about all of your medical conditions, including if you:

- have liver or kidney problems.
- take any other medicines, especially ones called TZDs (thiazolidinediones).
- have heart failure or other heart problems. If you have heart failure, it may get worse while you take TZDs with Insulin Lispro Protamine and Insulin Lispro Mix75/25.
- are pregnant or plan to become pregnant. Talk with your healthcare provider about the best way to control your blood sugar if you plan to become pregnant or while you are pregnant.
- are breastfeeding or plan to breastfeed. Talk with your healthcare provider about the best way to feed your baby while taking Insulin Lispro Protamine and Insulin Lispro Mix75/25.

Tell your healthcare provider about all the medicines you take, including prescription and over-the-counter medicines, vitamins, and herbal supplements.
Before you start taking Insulin Lispro Protamine and Insulin Lispro Mix75/25, talk to your healthcare provider about low blood sugar and how to manage it.

How should I take Insulin Lispro Protamine and Insulin Lispro Mix75/25?

- Read the Instructions for Use that comes with your Insulin Lispro Protamine and Insulin Lispro Mix75/25.
- Take Insulin Lispro Protamine and Insulin Lispro Mix75/25 exactly as your healthcare provider tells you to. Your healthcare provider should tell you how much Insulin Lispro Protamine and Insulin Lispro Mix75/25 to take and when to take it.
- Insulin Lispro Protamine and Insulin Lispro Mix75/25 starts acting fast. Inject Insulin Lispro Protamine and Insulin Lispro Mix75/25 within 15 minutes before you eat a meal.
- Know the type, strength, and amount of insulin you take. Do not change the type or amount of insulin you take unless your healthcare provider tells you to. The amount of insulin and the best time for you to take your insulin may need to change if you take different types of insulin.
- Check your insulin label each time you give your injection to make sure you are taking the correct insulin.
- Inject Insulin Lispro Protamine and Insulin Lispro Mix75/25 under the skin (subcutaneously) of your stomach area (abdomen), buttocks, upper legs or upper arms. Do not inject Insulin Lispro Protamine and Insulin Lispro Mix75/25 into your vein (intravenously) or use in an insulin infusion pump.
- Change (rotate) your injection sites within the area you choose with each dose to reduce your risk of getting lipodystrophy (pits in skin or thickened skin) and localized cutaneous amyloidosis (skin with lumps) at the injection sites.
  - Do not use the exact same spot for each injection.
  - Do not inject where the skin has pits, is thickened, or has lumps.
  - Do not inject where the skin is tender, bruised, scaly or hard, or into scars or damaged skin.
- Do not mix Insulin Lispro Protamine and Insulin Lispro Mix75/25 with other insulins or liquids.
- Check your blood sugar levels. Ask your healthcare provider what your blood sugars should be and when you should check your blood sugar levels.

Keep Insulin Lispro Protamine and Insulin Lispro Mix75/25 and all medicines out of the reach of children.

Your dose of Insulin Lispro Protamine and Insulin Lispro Mix75/25 may need to change because of a:
• change in physical activity or exercise, weight gain or loss, increased stress, illness, change in diet, or because of other medicines you take.

What should I avoid while taking Insulin Lispro Protamine and Insulin Lispro Mix75/25?
While taking Insulin Lispro Protamine and Insulin Lispro Mix75/25 do not:

- drive or operate heavy machinery until you know how Insulin Lispro Protamine and Insulin Lispro Mix75/25 affects you.
- drink alcohol or take prescription or over-the-counter medicines that contain alcohol.

What are the possible side effects of Insulin Lispro Protamine and Insulin Lispro Mix75/25?
Insulin Lispro Protamine and Insulin Lispro Mix75/25 may cause serious side effects that can lead to death, including:

- low blood sugar (hypoglycemia). Signs and symptoms of low blood sugar may include:

- dizziness or light-headedness
- sweating
- confusion
- headache
- blurred vision

- slurred speech
- shakiness
- fast heartbeat
- anxiety, irritability or mood changes
- hunger

Your healthcare provider may prescribe a glucagon product for emergency use so that someone else can give you glucagon if your blood sugar becomes too low (severe hypoglycemia) and you are unable to take sugar by mouth.

- severe allergic reaction (whole body reaction). Get medical help right away, if you have any of these signs or symptoms of a severe allergic reaction:

- a rash over your whole body
- trouble breathing

- a fast heartbeat
- sweating

- low potassium in your blood (hypokalemia).
- heart failure. Taking certain diabetes pills called thiazolidinediones or “TZDs” with Insulin Lispro Protamine and Insulin Lispro Mix75/25 may cause heart failure in some people. This can happen even if you have never had heart failure or heart problems before. If you already have heart failure it may get worse while you take TZDs with Insulin Lispro Protamine and Insulin Lispro Mix75/25. Your healthcare provider should monitor you closely while you are taking TZDs with Insulin Lispro Protamine and Insulin Lispro Mix75/25. Tell your healthcare provider if you have any new or worse symptoms of heart failure including:

- shortness of breath
- swelling of your ankles or feet

- sudden weight gain

Treatment with TZDs and Insulin Lispro Protamine and Insulin Lispro Mix75/25 may need to be adjusted or stopped by your healthcare provider if you have new or worse heart failure.
Get emergency medical help if you have:

- trouble breathing
- shortness of breath
- fast heartbeat
- swelling of your face, tongue, or throat

- sweating
- extreme drowsiness
- dizziness
- confusion

The most common side effects of Insulin Lispro Protamine and Insulin Lispro Mix75/25 include:

- low blood sugar (hypoglycemia)
- reactions at your injection site
- skin thickening or pits at the injection site (lipodystrophy)

- weight gain
- swelling in your hands or feet
- itching
- rash

These are not all the possible side effects of Insulin Lispro Protamine and Insulin Lispro Mix75/25. Call your doctor for medical advice about side effects. You may report side effects to FDA at 1-800-FDA-1088.

General information about the safe and effective use of Insulin Lispro Protamine and Insulin Lispro Mix75/25.
Medicines are sometimes prescribed for purposes other than those listed in a Patient Information leaflet. Do not take Insulin Lispro Protamine and Insulin Lispro Mix75/25 for a condition for which it was not prescribed. Do not give Insulin Lispro Protamine and Insulin Lispro Mix75/25 to other people, even if they have the same symptoms that you have. It may harm them.
This Patient Information leaflet summarizes the most important information about Insulin Lispro Protamine and Insulin Lispro Mix75/25. If you would like more information, talk with your healthcare provider. You can ask your pharmacist or healthcare provider for information about Insulin Lispro Protamine and Insulin Lispro Mix75/25 that is written for health professionals.

What are the ingredients in Insulin Lispro Protamine and Insulin Lispro Mix75/25?
Active ingredients: insulin lispro
Inactive ingredients: dibasic sodium phosphate, glycerin, hydrochloric acid, metacresol, phenol, protamine sulfate, sodium hydroxide, zinc oxide (zinc ion), and Water for Injection, USP.
Humalog® Mix75/25™ and KwikPen® are trademarks of Eli Lilly and Company.
Manufactured by: Eli Lilly and Company, Indianapolis, IN 46285, USA, US License Number 1891
Copyright © 1999, 2023, Eli Lilly and Company. All rights reserved.
For more information, call 1-800-545-5979.

This Patient Information has been approved by the U.S. Food and Drug Administration.

Revised: 07/2023

ILPILIS7525-0002-PPI-20230721

KWIKPEN INSTRUCTIONS FOR USE

INSTRUCTIONS FOR USE

Insulin Lispro Protamine and Insulin Lispro [IHN-soo-lihn LIYS-proh] Mix75/25™ KwikPen®

injectable suspension, for subcutaneous use

3 mL single-patient-use pen (100 units per mL)

This product is HUMALOG® Mix75/25™ (insulin lispro protamine and insulin lispro).

Read this Instructions for Use before you start taking Insulin Lispro Protamine and Insulin Lispro Mix75/25 and each time you get another KwikPen. There may be new information. This information does not take the place of talking to your healthcare provider about your medical condition or your treatment.

Do not share your Insulin Lispro Protamine and Insulin Lispro Mix75/25 KwikPen with other people, even if the needle has been changed. You may give other people a serious infection or get a serious infection from them.

Insulin Lispro Protamine and Insulin Lispro Mix75/25 KwikPen (“Pen”) is a disposable single-patient-use prefilled pen containing 300 units of Insulin Lispro Protamine and Insulin Lispro Mix75/25.

- You can give yourself more than 1 dose from the Pen.
- By turning the Dose Knob, you can dial doses from 1 to 60 units in 1 unit increments.
- If your dose is more than 60 units, you will need to give yourself more than 1 injection.
- The Plunger only moves a little with each injection, and you may not notice that it moves. The Plunger will only reach the end of the cartridge when you have used all 300 units in the Pen.

People who are blind or have vision problems should not use this Pen without help from a person trained to use the Pen.

How to recognize your Insulin Lispro Protamine and Insulin Lispro Mix75/25 KwikPen

- Pen color: Dark blue
- Dose Knob: Dark blue
- Labels: White label with yellow stripe

Supplies you will need to give your injection

- Insulin Lispro Protamine and Insulin Lispro Mix75/25 KwikPen
- KwikPen compatible Needle (Becton, Dickinson and Company Pen Needles recommended)
- Alcohol swab
- Gauze

Preparing your Pen

- Wash your hands with soap and water.
- Check your Pen to make sure you are taking the right type of insulin. This is especially important if you use more than 1 type of insulin.
- Always use a new needle for each injection to help prevent infections and blocked needles. Do not reuse or share your needles with other people. You may give other people a serious infection or get a serious infection from them.

Step 1:

- Pull the Pen Cap straight off.
  - Do not remove the Pen Label.
- Wipe the Rubber Seal with an alcohol swab.
  - Do not attach the Needle before mixing.

Step 2:

- Gently roll the Pen between your hands at least 10 times.

Step 3:

- Move the Pen up and down (invert) at least 10 times.
  Mixing by rolling and inverting the Pen is important to make sure you get the right dose.
  After mixing Insulin Lispro Protamine and Insulin Lispro Mix75/25, inject your dose right away. If you wait to inject your dose, the insulin will need to be mixed again.

Step 4:

- Check the liquid in the Pen. Insulin Lispro Protamine and Insulin Lispro Mix75/25 should look white and cloudy after mixing. Do not use if it looks clear or has any lumps or particles in it.

Step 5:

- Select a new Needle.
- Pull off the Paper Tab from the Outer Needle Shield.

Step 6:

- Push the capped Needle straight onto the Pen and twist the Needle on until it is tight.

Step 7:

- Pull off the Outer Needle Shield. Do not throw it away.
- Pull off the Inner Needle Shield and throw it away.

Priming your Pen

Prime your Pen before each injection.

- Priming your Pen means removing the air from the Needle and Cartridge that may collect during normal use and ensures that the Pen is working correctly.
- If you do not prime before each injection, you may get too much or too little insulin.

Step 8:

- To prime your Pen, turn the Dose Knob to select 2 units.

Step 9:

- Hold your Pen with the Needle pointing up. Tap the Cartridge Holder gently to collect air bubbles at the top.

Step 10:

- Continue holding your Pen with Needle pointing up. Push the Dose Knob in until it stops, and “0” is seen in the Dose Window. Hold the Dose Knob in and count to 5 slowly.
- You should see insulin at the tip of the Needle.
  - If you do not see insulin, repeat priming steps 8 to 10, no more than 4 times.
  - If you still do not see insulin, change the Needle and repeat priming steps 8 to 10.

Small air bubbles are normal and will not affect your dose.

Selecting your dose

- You can give from 1 to 60 units in a single injection.
- If your dose is more than 60 units, you will need to give more than one injection.
  - If you need help with dividing up your dose the right way, ask your healthcare provider.
  - Use a new Needle for each injection and repeat the priming steps.

Step 11:

- Turn the Dose Knob to select the number of units you need to inject. The Dose Indicator should line up with your dose.
  - The Pen dials 1 unit at a time.
  - The Dose Knob clicks as you turn it.
  - Do not dial your dose by counting the clicks. You may dial the wrong dose. This may lead to you getting too much insulin or not enough insulin.
  - The dose can be corrected by turning the Dose Knob in either direction until the correct dose lines up with the Dose Indicator.
  - The even numbers (for example, 12) are printed on the dial.
  - The odd numbers, (for example, 25) after the number 1, are shown as full lines.
- Always check the number in the Dose Window to make sure you have dialed the correct dose.

(Example: 12 units shown in the Dose Window)
(Example: 25 units shown in the Dose Window)

- The Pen will not let you dial more than the number of units left in the Pen.
- If you need to inject more than the number of units left in the Pen, you may either:
  - inject the amount left in your Pen and then use a new Pen to give the rest of your dose, or
  - get a new Pen and inject the full dose.
- It is normal to see a small amount of insulin left in the Pen that you can not inject.

Giving your injection

- Inject your insulin as your healthcare provider has shown you.
- Change (rotate) your injection sites within the area you choose for each dose to reduce your risk of getting lipodystrophy (pits in skin or thickened skin) and localized cutaneous amyloidosis (skin with lumps) at the injection sites.
- Do not inject where the skin has pits, is thickened, or has lumps.
- Do not inject where the skin is tender, bruised, scaly or hard, or into scars or damaged skin.
- Do not try to change your dose while injecting.

Step 12:

- Choose your injection site.
  Insulin Lispro Protamine and Insulin Lispro Mix75/25 is injected under the skin (subcutaneously) of your stomach area, buttocks, upper legs or upper arms.
- Wipe your skin with an alcohol swab, and let your skin dry before you inject your dose.

Step 13:

- Insert the Needle into your skin.
- Push the Dose Knob all the way in.
- Continue to hold the Dose Knob in and slowly count to 5 before removing the Needle.
  Do not try to inject your insulin by turning the Dose Knob. You will not receive your insulin by turning the Dose Knob.

Step 14:

- Pull the Needle out of your skin.
  A drop of insulin at the Needle tip is normal. It will not affect your dose.
- Check the number in the Dose Window.
  - If you see “0” in the Dose Window, you have received the full amount you dialed.
  - If you do not see “0” in the Dose Window, do not redial. Insert the Needle into your skin and finish your injection.
  - If you still do not think you received the full amount you dialed for your injection, do not start over or repeat the injection. Monitor your blood glucose as instructed by your healthcare provider.
  - If you normally need to give 2 injections for your full dose, be sure to give your second injection.

The Plunger only moves a little with each injection, and you may not notice that it moves.
If you see blood after you take the Needle out of your skin, press the injection site lightly with a piece of gauze or an alcohol swab. Do not rub the area.

After your injection

Step 15:

- Carefully replace the Outer Needle Shield.

Step 16:

- Unscrew the capped Needle and throw it away (see Disposing of Pens and Needles section).
- Do not store the Pen with the Needle attached to prevent leaking, blocking the Needle, and air from entering the Pen.

Step 17:

- Replace the Pen Cap by lining up the Cap Clip with the Dose Indicator and pushing straight on.

Disposing of Pens and Needles

- The used Pen may be discarded in your household trash after you have removed the needle.
- Put your used needles in a FDA-cleared sharps disposal container right away after use. Do not throw away (dispose of) loose needles in your household trash.
- If you do not have a FDA-cleared sharps disposal container, you may use a household container that is:
  - made of a heavy-duty plastic,
  - can be closed with a tight-fitting, puncture-resistant lid, without sharps being able to come out,
  - upright and stable during use,
  - leak-resistant, and
  - properly labeled to warn of hazardous waste inside the container.
- When your sharps disposal container is almost full, you will need to follow your community guidelines for the right way to dispose of your sharps disposal container. There may be state or local laws about how you should throw away used needles and syringes. For more information about safe sharps disposal, and for specific information about sharps disposal in the state that you live in, go to the FDA's website at: http://www.fda.gov/safesharpsdisposal
- Do not dispose of your used sharps disposal container in your household trash unless your community guidelines permit this. Do not recycle your used sharps disposal container.

Storing your Pen

Unused Pens

- Store unused Pens in the refrigerator at 36°F to 46°F (2°C to 8°C).
- Do not freeze your insulin. Do not use if Insulin Lispro Protamine and Insulin Lispro Mix75/25 has been frozen.
- Unused Pens may be used until the expiration date printed on the Label, if the Pen has been kept in the refrigerator.
- Unused Pens stored at room temperature, up to 86°F (30°C), should be thrown away after 10 days.

In-use Pen

- Store the Pen you are currently using at room temperature [up to 86°F (30°C)]. Keep away from heat and light.
- Throw away the Insulin Lispro Protamine and Insulin Lispro Mix75/25 Pen you are using after 10 days, even if it still has insulin left in it.

General information about the safe and effective use of your Pen

- Keep your Pen and needles out of the reach of children.
- Do not use your Pen if any part looks broken or damaged.
- Always carry an extra Pen in case yours is lost or damaged.

Troubleshooting

- If you can not remove the Pen Cap, gently twist the cap back and forth, and then pull the cap straight off.
- If the Dose Knob is hard to push:
  - Pushing the Dose Knob more slowly will make it easier to inject.
  - Your Needle may be blocked. Put on a new Needle and prime the Pen.
  - You may have dust, food, or liquid inside the Pen. Throw the Pen away and get a new Pen.

If you have any questions or problems with your Insulin Lispro Protamine and Insulin Lispro Mix75/25 KwikPen, contact Lilly at 1-800-LillyRx (1-800-545-5979) or call your healthcare provider for help.

Manufactured by:

Eli Lilly and Company
Indianapolis, IN 46285, USA

US License Number 1891

This Instructions for Use has been approved by the U.S. Food and Drug Administration.

Revised: 07/2023

Humalog® Mix75/25™ and KwikPen® are trademarks of Eli Lilly and Company.

Copyright © 2007, 2023, Eli Lilly and Company. All rights reserved.

Insulin Lispro Protamine and Insulin Lispro Mix75/25 KwikPen meets the current dose accuracy and functional requirements of ISO 11608-1.

ILPILIS7525KP-0003-IFU-20230721

PACKAGE LABEL

PACKAGE CARTON – Insulin Lispro Protamine and Insulin Lispro Injectable Suspension KwikPen Mix75/25™ 5ct

NDC 0002-8233-05

Insulin Lispro Protamine and Insulin Lispro KwikPen Mix75/25™ Injectable Suspension

For Single Patient Use Only

Dispense in this sealed carton.

Needles not included

100 units per mL (U-100)

This device is recommended for use with Becton, Dickinson and Company's insulin pen needles

For subcutaneous use only.

prefilled insulin delivery device

Rx only

This product is Humalog Mix75/25.

5 x 3 mL Prefilled Pens

Read Insulin Delivery Device Instructions for Use